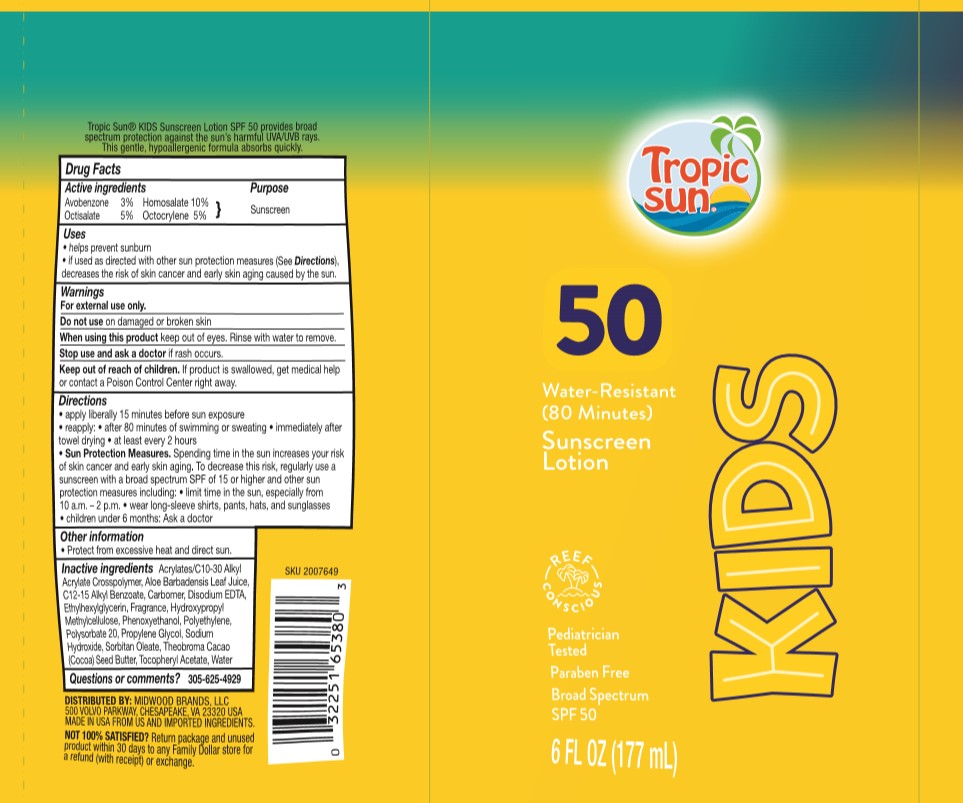 DRUG LABEL: Tropic Sun
NDC: 58443-0397 | Form: LOTION
Manufacturer: Prime Enterprises, Inc.
Category: otc | Type: HUMAN OTC DRUG LABEL
Date: 20210205

ACTIVE INGREDIENTS: HOMOSALATE 99.2 mg/1 mL; OCTISALATE 49.6 mg/1 mL; OCTOCRYLENE 49.6 mg/1 mL; AVOBENZONE 29.76 mg/1 mL
INACTIVE INGREDIENTS: EDETATE DISODIUM ANHYDROUS; ETHYLHEXYLGLYCERIN; CARBOMER INTERPOLYMER TYPE A (ALLYL SUCROSE CROSSLINKED); ALKYL (C12-15) BENZOATE; CARBOMER HOMOPOLYMER, UNSPECIFIED TYPE; HYPROMELLOSES; PROPYLENE GLYCOL; ALOE VERA LEAF; FRAGRANCE FRESH CITRUS FLORAL ORC1501495; PHENOXYETHANOL; POLYSORBATE 20; SODIUM HYDROXIDE; ALPHA-TOCOPHEROL ACETATE; HIGH DENSITY POLYETHYLENE; SORBITAN MONOOLEATE; COCOA BUTTER; WATER

Tropic Sun SPF 50 Sunscreen Lotion Kids

Active ingredients

Avobenzone 3%

Homosalate 10%

Octisalate 5%

Octocrylene 5%

Purpose

Sunscreen

Uses

helps prevent sunburn

if used as directed with other sun protection measures (see Directions), decreases the risk of skin cancer and early skin aging caused by the sun.

Warnings

For external use only.

Do not use

on damaged or broken skin

When using this product

keep out of eyes. Rinse with water to remove.

Stop use and ask a doctor

if rash occurs.

Keep out of reach of children.

if product is swallowed, get medical help or contact a Poison Control Center right away.

Directions

apply liberally 15 minutes before sun exposure

reapply:

after 80 minutes of swimming or sweating

immediately after towel drying

at least every 2 hours

Sun Protection Measures. Spending time in the sun increases your risk of skin cancer and early skin aging. To decrease this risk, regularly use a sunscreen with a broad spectrum SPF of 15 or higher and other sun protection measures including:

limit time in the sun, especially from 10 a.m. - 2 p.m.

wear long-sleeve shirts, pants, hats, and sunglasses

children under 6 months: Ask a doctor

Other information

Protect form excessive heat and direct sun.

Inactive ingredients

Acrylates/C10-30 Alkyl Acrylate Crosspolymer, Aloe Barbadensis Leaf Juice, C12-15 Alkyl Benzoate, Carbomer, Disodium EDTA, Ethylhexylglycerin, Fragrance, Hydroxypropyl Methylcellulose, Phenoxyethanol, Polyethylene, Polysorbate 20, Propylene Glycol, Sodium Hydroxide, Sorbitan Oleate, Theobroma Cacao (Cocoa) Seed Butter, Tocopheryl Acetate, Water

Questions or comments?

305-625-4929